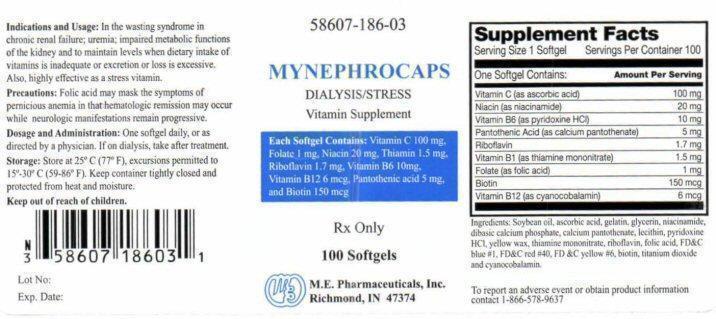 DRUG LABEL: MYNEPHROCAPS
NDC: 58607-186 | Form: CAPSULE
Manufacturer: MARTIN EKWEALOR PHARMACEUTICALS, INC.
Category: prescription | Type: HUMAN PRESCRIPTION DRUG LABEL
Date: 20131213

ACTIVE INGREDIENTS: ASCORBIC ACID 100 mg/1 1; NIACINAMIDE 20 mg/1 1; PYRIDOXINE HYDROCHLORIDE 10 mg/1 1; CALCIUM PANTOTHENATE 5 mg/1 1; RIBOFLAVIN 1.7 mg/1 1; THIAMINE MONONITRATE 1.5 mg/1 1; FOLIC ACID 1 mg/1 1; BIOTIN 150 ug/1 1; CYANOCOBALAMIN 6 ug/1 1
INACTIVE INGREDIENTS: SOYBEAN OIL; GELATIN; GLYCERIN; CALCIUM PHOSPHATE, DIBASIC, ANHYDROUS; LECITHIN, SOYBEAN; YELLOW WAX; FD&C BLUE NO. 1; FD&C RED NO. 40; FD&C YELLOW NO. 6; TITANIUM DIOXIDE

Supplemental Facts

Serving Size 1 Softgel Serving Per Container 100
One Softgel Contains: Amount Per Serving
Vitamin C (as ascorbic acid) 100 mg
Niacin (as niacinamide) 20 mg
Vitamin B (as pyridoxine HCL) 10 mg
Pantotnenic Acid (as calcium pantothenate) 5 mg
Riboflavin 1.7 mg
Vitamin B1 (as thiamine mononitrate) 1.5 mg
Folate (as folic acid) 1 mg
Biotin 150 mcg
Vitamin B12 (as cyanocobalamin) 6 mcg

Indications and Usage:

In the wasting syndrome in chronic renal failure; uremia; impaired metabolic functions of the kidney and to maintain levels when dietary intake of vitamins is inadequate or excretion or loss in excessive.
Also, highly effective as a stress vitamin.

Precautions:

Folic acid may mask the symptoms of pernicious anemia in that hematologic remission may occur while neurologic manifestations remain progressive.

Dosage and Administration:

One softgel daily, or as directed by a physician. If on dialysis, take after treatment.

Storage:

Store at 25° C (77° F), excursions permitted to 15° - 30° C (59- 80° F). Keep container tightly closed and protected from heat and moisture.

Keep out of reach of children.

Ingredients:

Soybean oil, ascorbic acid, gelatin, glycerin, niacinamide, diabasic calcium phosphate, calcium pantothenate, lecithin, pyridoxineHCL, yellow wax, thiamine monitrate, riboflavin, folic acid, FD and c blue #1, FD and C red #40, FD and C yellow #6, biotin, titanium dioxide and cyanocobalamin.

To report any adverse event or obtain product information contact 1-866-578-9637

Product Label

58607-186-03
MYNEPHOCAPS
DIALYSIS/STRESS
Vitamin Supplement
Each Softgel Contains: Vitamin C 100 mg, Folate 1 mg, Niacin 20 mg, Thiamine 1.5 mg, Riboflavin 1.7 mg, Vitamin B6 10 mg, Vitamin B12 6 mcg, Pantothenic acid 5 mg, and Biotin 150 mcg
Rx Onlt
100 Softgels
M.E. Pharmaceuticals, Inc.Richmond, IN 47374
Lot No:
Exp Date: